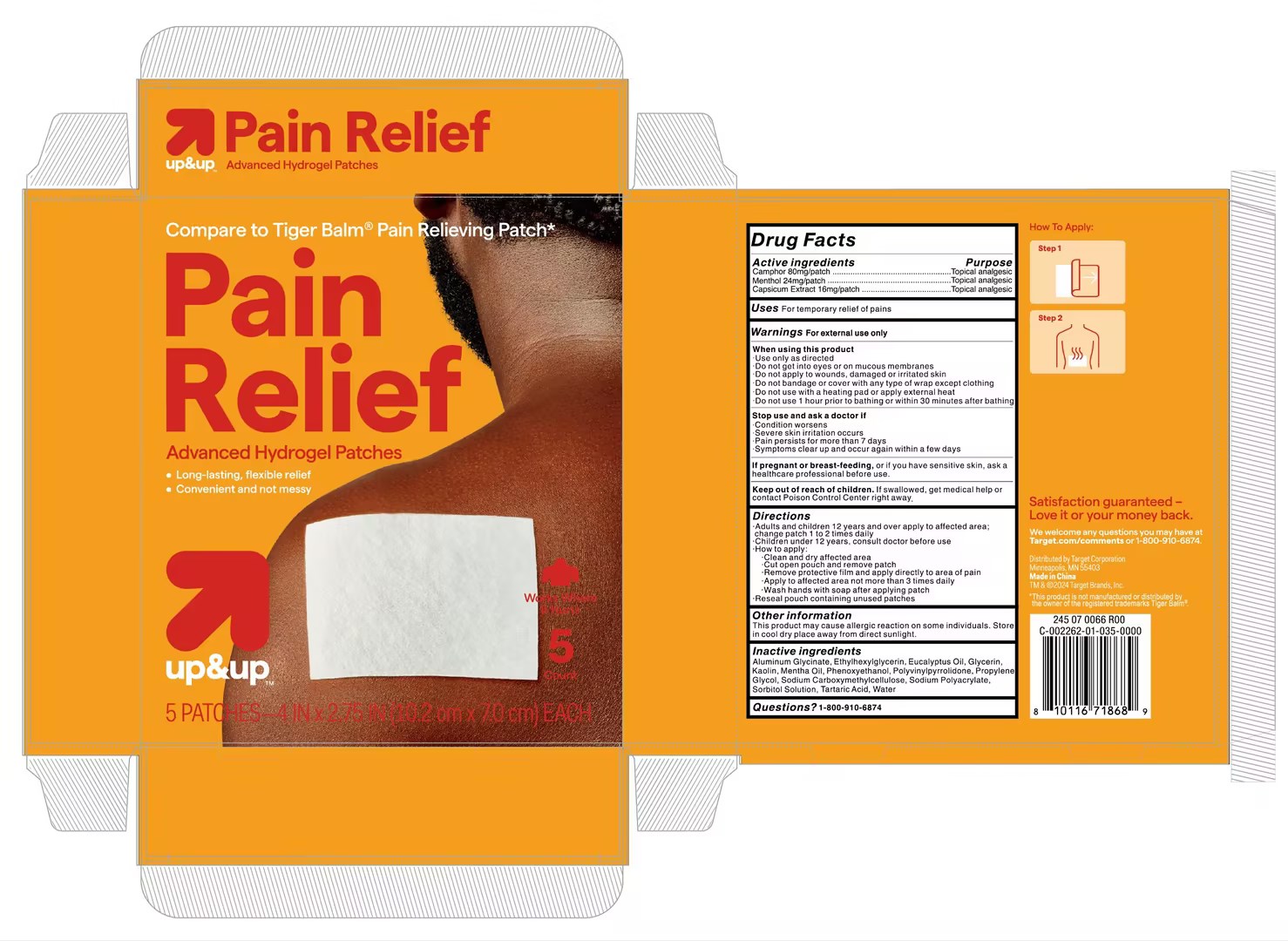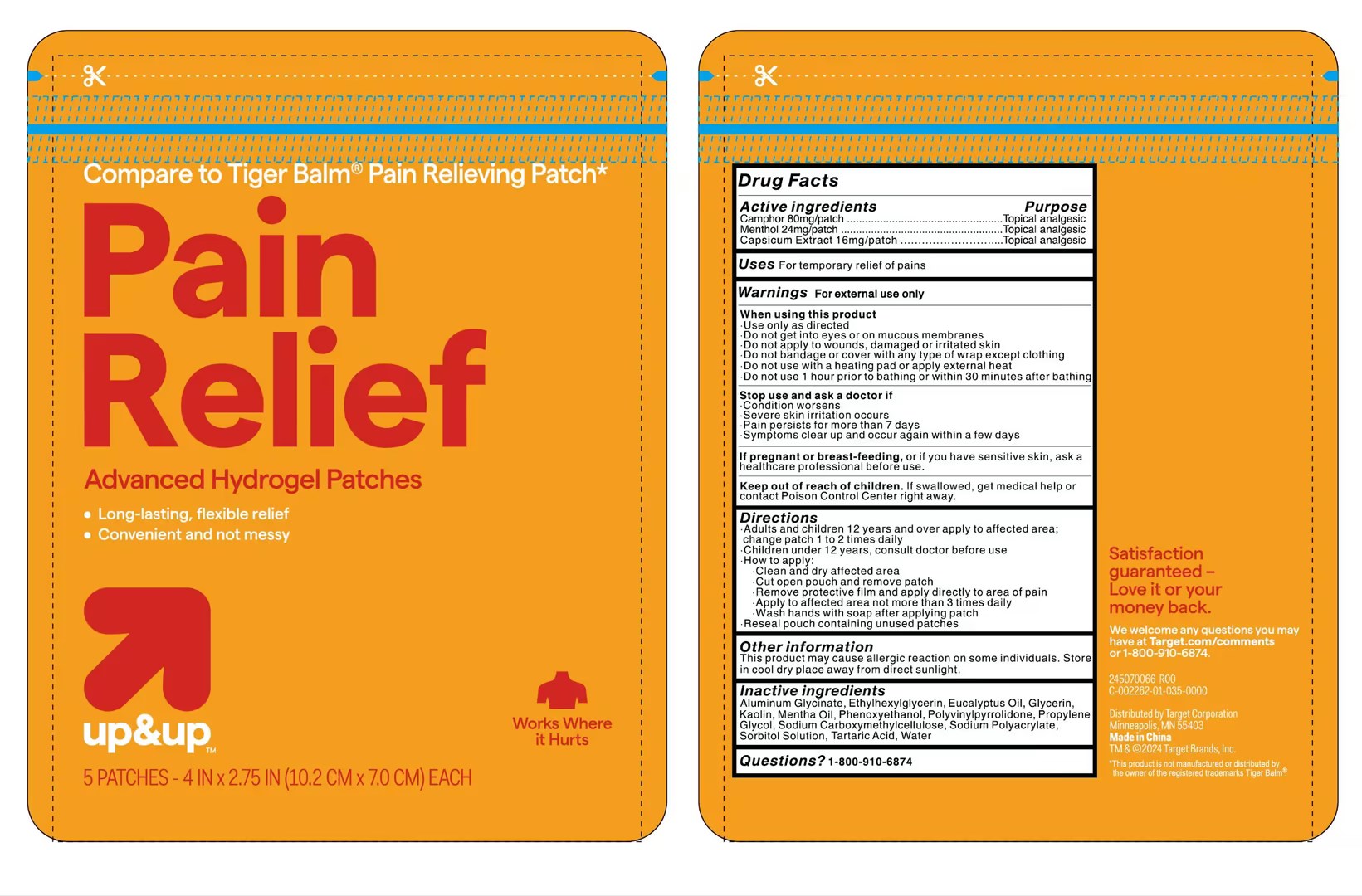 DRUG LABEL: Pain Relief Patch
NDC: 78691-141 | Form: PATCH
Manufacturer: QUEST USA CORP.
Category: otc | Type: HUMAN OTC DRUG LABEL
Date: 20251231

ACTIVE INGREDIENTS: CAMPHOR (SYNTHETIC) 80 mg/100 1; MENTHOL 24 mg/100 1; NONIVAMIDE 16 mg/100 1
INACTIVE INGREDIENTS: DIHYDROXYALUMINUM AMINOACETATE ANHYDROUS; ETHYLHEXYLGLYCERIN; KAOLIN; CARBOXYMETHYLCELLULOSE SODIUM, UNSPECIFIED FORM; SORBITOL SOLUTION; TARTARIC ACID; EUCALYPTUS OIL; POVIDONE; PEPPERMINT OIL; PROPYLENE GLYCOL; PHENOXYETHANOL; GLYCERIN; SODIUM ACRYLATE; WATER

78691-141

Active Ingredient

CAMPHOR (SYNTHETIC) 80mg
MENTHOL 24mg
NONIVAMIDE 16mg

Purpose

Topical analgesic

Use

For temporary relief of pains

Warnings

For external use only

Do not use

·Do not get into eyes or on mucous membranes
·Do not apply to wounds, damaged or irritated skin
·Do not bandage or cover with any type of wrap except clothing
·Do not use with a heating pad or apply external heat
·Do not use 1 hour prior to bathing or within 30 minutes after bathing

Stop Use

Stop use and ask a doctor if
·Condition worsens
·Severe skin irritation occurs
·Pain persists for more than 7 days
·Symptoms clear up and occur again within a few days

When Using

When using this product·Use only as directed

Ask Doctor

If pregnant or breast-feeding, or if you have sensitive skin, ask a healthcare professional before use.
Children under 12 years, consult doctor before use

Keep out of reach of children. If swallowed, get medical help or contact Poison Control Center right away.

Directions

·Adults and children 12 years and over apply to affected area; change patch 1 to 2 times daily
·Children under 12 years, consult doctor before use
How to apply:
·Clean and dry affected area
·Cut open pouch and remove patch
·Remove protective film and apply directly to area of pain
·Apply to affected area not more than 3 times daily
·Wash hands with soap after applying patch
·Reseal pouch containing unused patches

Other information

This product may cause allergic reaction on some individuals.Store in cool dry place away from direct sunlight.

Inactive ingredients

Aluminum Glycinate, Ethylhexylglycerin, Eucalyptus Oil, Glycerin, Kaolin, Mentha Oil, Phenoxyethanol, Polyvinylpyrrolidone,Propylene Glycol, Sodium Carboxymethylcellulose, Sodium Polyacrylate, Sorbitol Solution, Tartaric Acid, Water

Questions

1-800-910-6874